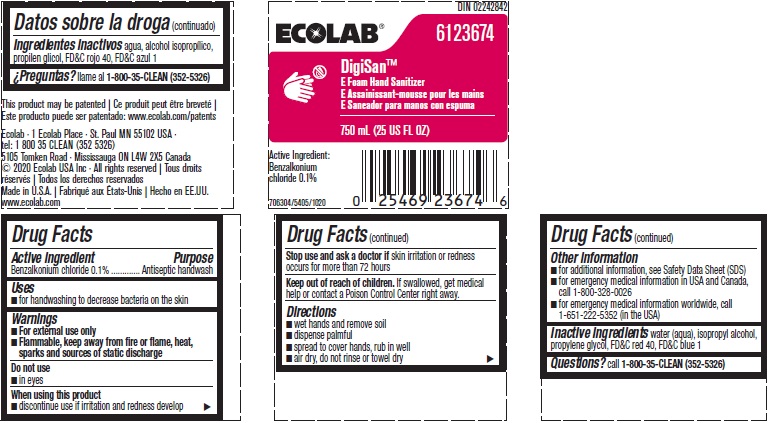 DRUG LABEL: DigiSan E
NDC: 47593-404 | Form: SOLUTION
Manufacturer: Ecolab Inc.
Category: otc | Type: HUMAN OTC DRUG LABEL
Date: 20240328

ACTIVE INGREDIENTS: BENZALKONIUM CHLORIDE 1 mg/1 mL
INACTIVE INGREDIENTS: WATER; ISOPROPYL ALCOHOL; PROPYLENE GLYCOL; FD&C RED NO. 40; FD&C BLUE NO. 1

Drug Facts

Active ingredient

Benzalkonium chloride, 0.1%

Purpose

Antiseptic handwash

Uses

- for handwashing to decrease bacteria on the skin

Warnings

- For external use only
- Flammable, keep away from fire or flame, heat sparks and sources of static discharge

Do not use

- In eyes

When using this product

- Discontinue use if irritation and redness develop

Stop use and ask a doctor if

- Skin irritation or redness occurs for more than 72 hours

Keep out of reach of children.

If swallowed, get medical help or contact a Poison Control Center right away.

Directions

- wet hands and remove soil
- dispense palmful
- spread to cover hands, rub in well
- air dry, do not rinse or towel dry

Other Information

- For additional information, see Safety Data Sheet (SDS)
- For emergency medical information in USA and Canada, call 1-800-328-0026
- For emergency medical information worldwide, call 1-651-222-5352 (in USA)

Inactive ingredients:

water (aqua), isopropyl alcohol, propylene glycol, FD&C red 40, F&DC blue 1

Questions?

Call 1-800-35-CLEAN (352-5326)

Principal Display Panel/Representative Label

ECOLAB

6123674

DigiSan™

E Foam Hand Sanitizer

750 mL (25 US FL OZ)

Active Ingredient:

Benzalkonium chloride 0.1%

706304/5405/1020

This product may be patented

www.ecolab.com/patents

Ecolab · 1 Ecolab Place · St. Paul MN 55102 USA · tel: 1 800 35 CLEAN (352 5326)

5105 Tomken Road · Mississauga ON L4W 2X5 Canada

© 2020 Ecolab USA Inc · All rights reserved

Made in U.S.A.

www.ecolab.com